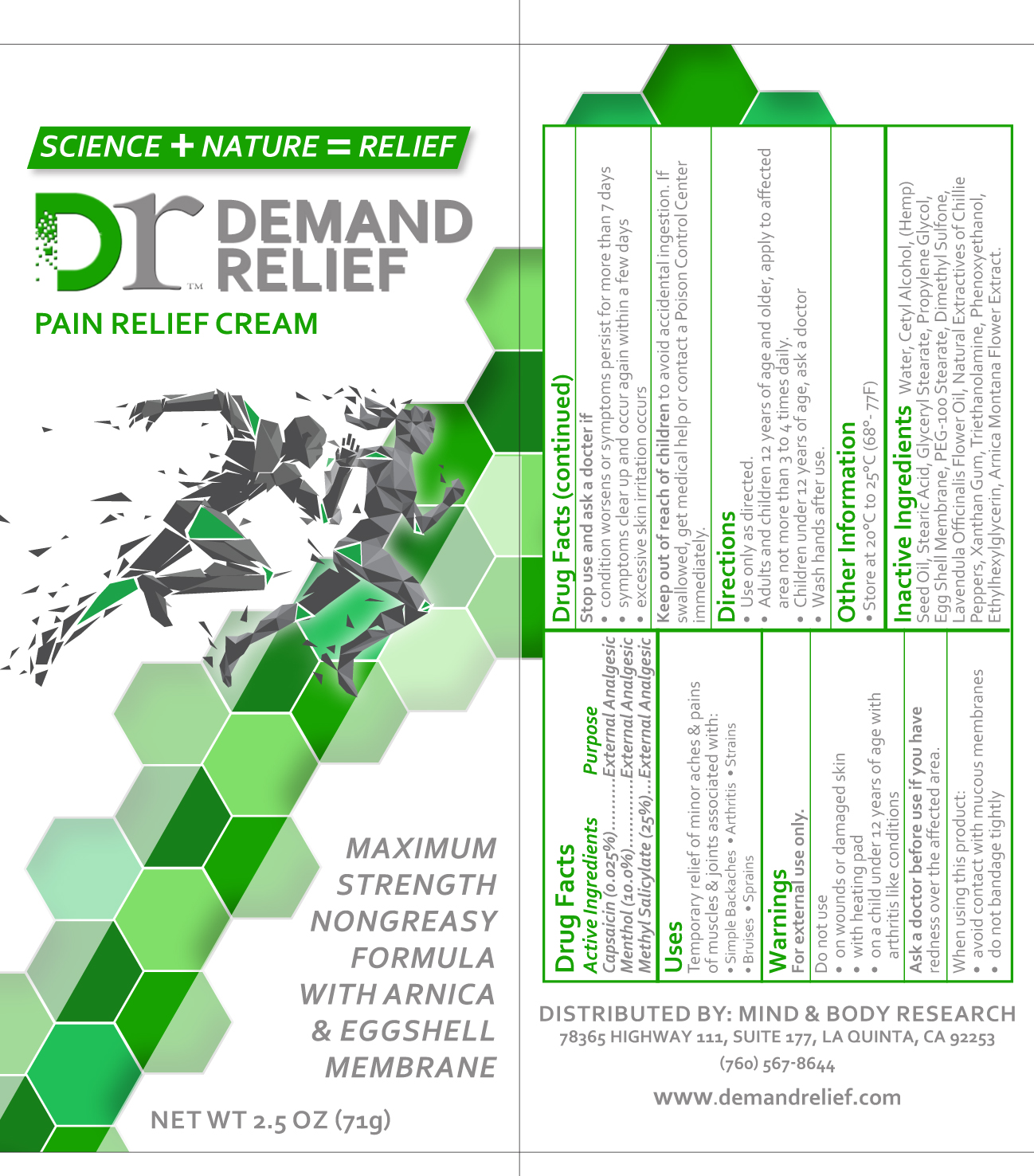 DRUG LABEL: Dr Demand Relief Pain Relief
NDC: 72185-225 | Form: CREAM
Manufacturer: Mind and Body Research Corp
Category: otc | Type: HUMAN OTC DRUG LABEL
Date: 20190227

ACTIVE INGREDIENTS: METHYL SALICYLATE 25 g/100 g; CAPSAICIN 0.025 g/100 g; MENTHOL 10 g/100 g
INACTIVE INGREDIENTS: CANNABIS SATIVA SEED OIL; STEARIC ACID; LAVENDER OIL; PROPYLENE GLYCOL; EGG SHELL MEMBRANE; WATER; PEG-100 STEARATE; DIMETHYL SULFONE; XANTHAN GUM; GLYCERYL MONOSTEARATE; TROLAMINE; PHENOXYETHANOL; ETHYLHEXYLGLYCERIN; ARNICA MONTANA FLOWER; CETYL ALCOHOL

Dr Demand Relief Pain Relief Cream

Active Ingredients Purpose
Capsaicin (0.025%)..........External Analgesic
Menthol (10.o%).............External Analgesic
Methyl Salicylate (25%)...External Analgesic

Uses
Temporary relief of minor aches & pains
of muscles & joints associated with:
• Simple Backaches • Arthritis • Strains
• Bruises • Sprains

Keep out of reach of children to avoid accidental ingestion. If
swallowed, get medical help or contact a Poison Control Center
immediately.

Warnings
For external use only.
Do not use
• on wounds or damaged skin
• with heating pad
• on a child under 12 years of age with
arthritis like conditions
Ask a doctor before use if you have
redness over the affected area.
When using this product:
• avoid contact with mucous membranes
• do not bandage tightly

Directions
• Use only as directed.
• Adults and children 12 years of age and older, apply to affected
area not more than 3 to 4 times daily.
• Children under 12 years of age, ask a doctor
• Wash hands after use.

INACTIVE INGREDIENT

Inactive Ingredients Water, Cetyl Alcohol, (Hemp)Seed Oil, Stearic Acid, Glyceryl Stearate, Propylene Glycol,
Egg Shell Membrane, PEG-100 Stearate, Dimethyl Sulfone, Lavendula Officinalis Flower Oil, Natural Extractives of Chillie
Peppers, Xanthan Gum, Triethanolamine, Phenoxyethanol, Ethylhexylglycerin, Arnica Montana Flower Extract.

Stop use and ask a docter if
• condition worsens or symptoms persist for more than 7 days
• symptoms clear up and occur again within a few days
• excessive skin irritation occurs

PACKAGE LABEL

Dr Demand Relief

Pain Relief Cream

Developed with Propietary ingredients